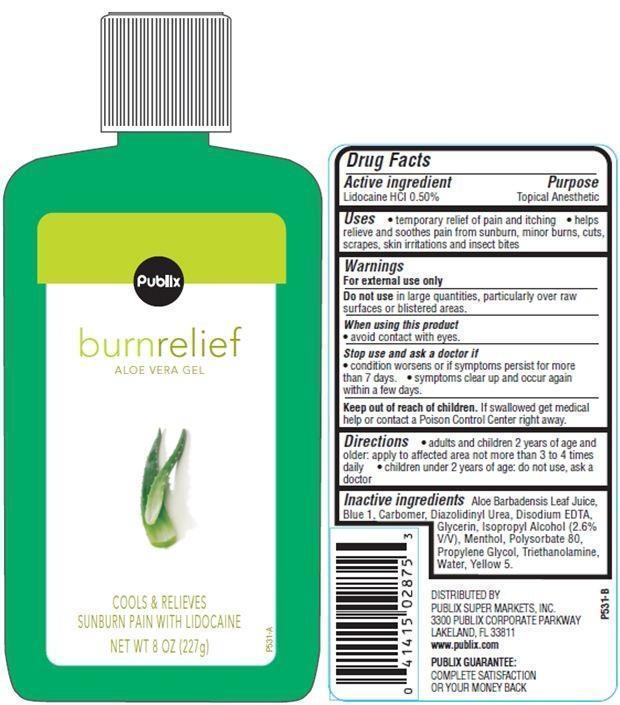 DRUG LABEL: Publix Burn Relief 
NDC: 56062-701 | Form: GEL
Manufacturer: Publix Super Markets Inc
Category: otc | Type: HUMAN OTC DRUG LABEL
Date: 20121115

ACTIVE INGREDIENTS: LIDOCAINE HYDROCHLORIDE 0.5 g/100 g
INACTIVE INGREDIENTS: ALOE VERA LEAF; FD&C BLUE NO. 1; DIAZOLIDINYL UREA; EDETATE DISODIUM; GLYCERIN; MENTHOL; POLYSORBATE 80; PROPYLENE GLYCOL; TROLAMINE; WATER; FD&C YELLOW NO. 5

Drug Facts

Active ingredient

Lidocaine HCL 0.50%

Purpose

Topical Anesthetic

Uses

- temporary relief of pain and itching
- helps relieve and soothes pain from sunburn, minor burns,cuts,scrapes, skin irritations and inspect bites

Warnings

For external use only

Do not use in large quantities,particularly over raw surfaces or blistered areas.

When using this product

- avoid contact with eyes.

Stop use and ask a doctor if

- condition worsens or symptoms persist for more than 7 days.
- symptoms clear up and occur again within a few days.

Keep out of reach of children.
If swallowed get medical help or contact Poison Control Center immediately.

Directions

- adults and children 2 years of age and older: apply to affected area not more than 3 to 4 times daily
- children under 2 years of age: do not use, ask a doctor

Inactive ingredients

Water, Propylene Glycol, Glycerin, Isopropyl Alcohol, Triethanolamine, Polysorbate 80, Carbomer, Aloe Barbadensis Leaf Juice, Menthol, Disodium EDTA, Diazolidinyl Urea, Yellow 5, Blue 1.

Principal Display Panel

Publix
burnreilef
ALOE VERA GEL
COOLS AND RELIEVES
SUNBURN PAIN WITH LIDOCAINE
NET WT 8 OZ(227g)